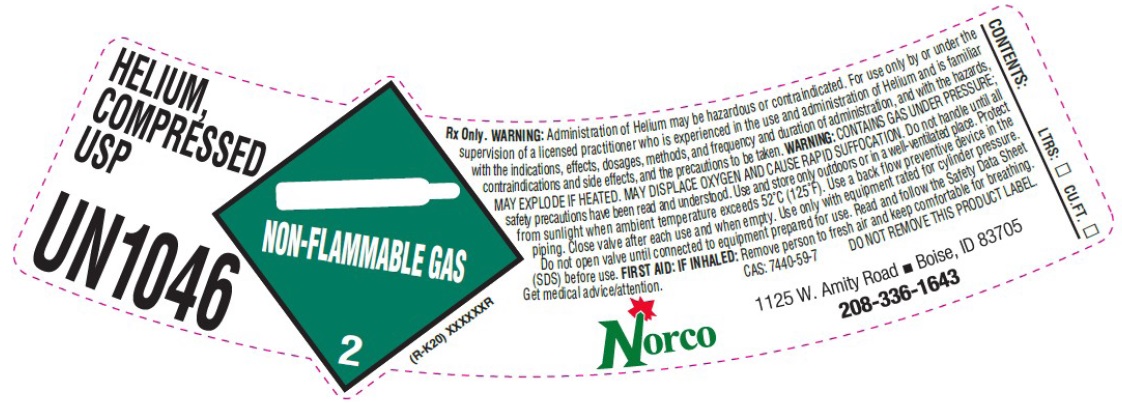 DRUG LABEL: HELIUM
NDC: 42602-002 | Form: GAS
Manufacturer: Norco, Inc.
Category: prescription | Type: HUMAN PRESCRIPTION DRUG LABEL
Date: 20250831

ACTIVE INGREDIENTS: HELIUM 99 L/100 L

HELIUM COMPRESSED USP LABEL

Helium
Compressed
USP
UN1046 ((RK-20) XXXXXXR

Rx Only. WARNING: Administration of Helium may be hazardous or contraindicated. For use
only by or under the supervision of a licensed practitioner who is experienced in the use and
administration of Helium and is familiar with the indications, effects, dosages, methods, and
frequency and duration of administration, and with the hazards, contraindications and side
effects, and the precautions to be taken. WARNING: CONTAINS GAS UNDER PRESSURE; MAY EXPLODE
IF HEATED. MAY DISPLACE OXYGEN AND CAUSE RAPID SUFFOCATION. Do not handle until all safety
precautions have been read and understood. Use and store only outdoors or in a well-ventilated place. Protect from sunlight when ambient temperature exceeds 52º C (125º F).Use a back flow preventive device in the piping. Close valve after each use and when empty. Use only with equipment rated for cylinder pressure. Do not open valve until connected to equipment prepared for use. Read
and follow the Safety Data Sheet (SDS) before use. FIRST AID: IF INHALED: Remove person to fresh air and keep
comfortable for breathing. Get medical advice/attention. CAS 7440-59-7 DO NOT REMOVE THIS PRODUCT LABEL

Norco
1125 W. Amity Rd. • Boise, ID 83705
208-336-1643

CONTENTS

LTRS: __

CU.FT. __

res